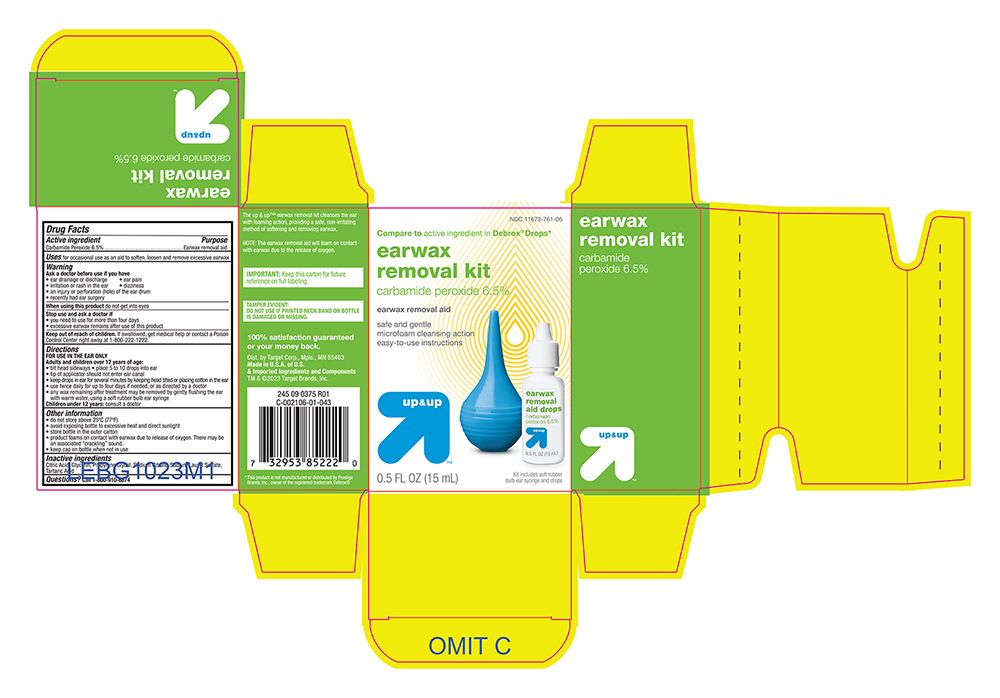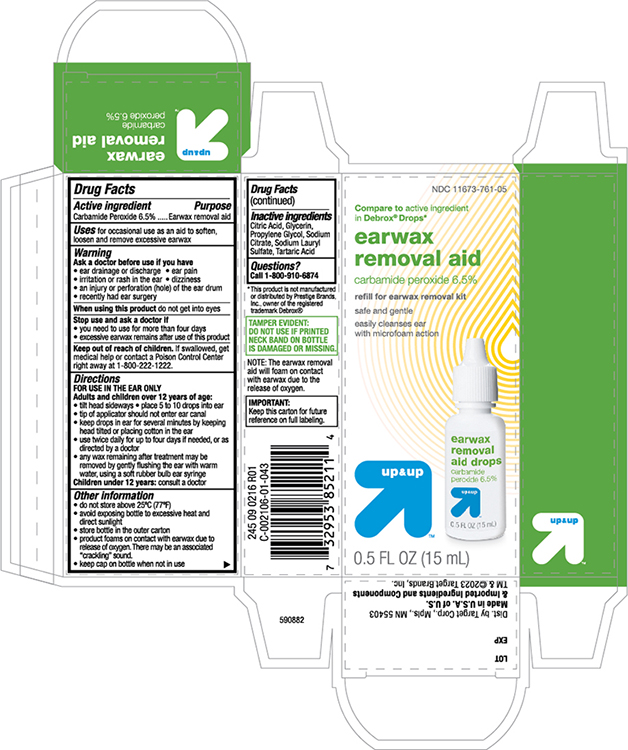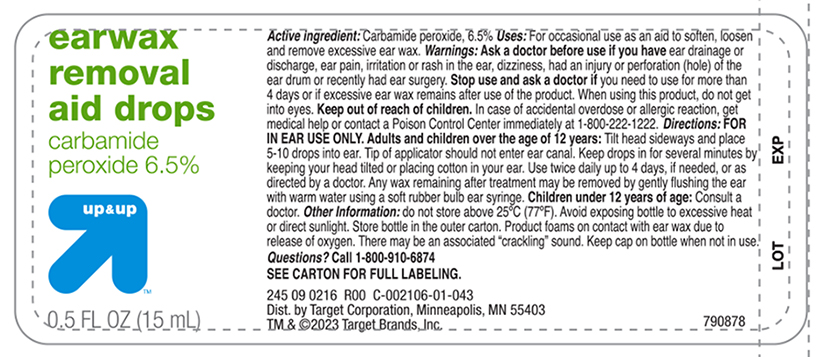 DRUG LABEL: Ear Wax Removal Drops
NDC: 11673-761 | Form: SOLUTION/ DROPS
Manufacturer: Target Corporation
Category: otc | Type: HUMAN OTC DRUG LABEL
Date: 20241121

ACTIVE INGREDIENTS: CARBAMIDE PEROXIDE 65 mg/1 mL
INACTIVE INGREDIENTS: GLYCERIN; ANHYDROUS CITRIC ACID; PROPYLENE GLYCOL; sodium citrate; SODIUM LAURYL SULFATE; TARTARIC ACID

Active Ingredient

Carbamide Peroxide 6.5%

Purpose

Earwax Removal Aid

Uses

For occasional use as an aid to soften, loosen and remove excessive ear wax.

Warnings

Ask a Doctor before use if you have

- eardrainage, discharge, ear pain,irritation
- rash in the ear,or are dizzy
- injury or perforation (hole) of the ear drum
- Recently had ear surgery

Stop Use and Ask a Doctor if

- you need to use for more than 4 days
- execessive ear wax remain after use of this product

When Using this Product

- do not use for more than four days
- avoid contact with the eyes. If accidental contact with the eyes occurs, flush eyes with water and consult a doctor
- if excessive earwax remains after the use of this product, consult a doctor

Keep out of the reach of children

If swallowed, get medical help or contact a Poison Control Center right away.

Directions FOR USE IN THE EAR ONLY

Adults and children over 12 years of age:

- Tilt head sideways and place 5 to 10 drops into ear.
- Tip of applicator should not enter ear canal.
- Keep drops in ear for several minutes by keeping head tilted or placing cotton in the ear.
- Use twice daily for up to 4 days if needed, or as directed by a doctor.
- Any earwax remaining after treatment may be removed by gently flushing the ear with warm water, using a soft rubber bulb ear syringe.
- When the ear canal is irrigated, the tip of the ear syringe should not obstruct the flow of water leaving the ear canal.

Children under 12 years: consult a doctor.

Other Information

- Protect from heat and direct sunlight
- product foams on contact with ear wax due ot releae of oxygen, there may be associated cracking
- Keep cap on bottle when not in use.
- Lot No. and EXP date: see label, bottom container or box.

Inactive Ingredients

Citric Acid, Glycerin, Propylene Glycol, Sodium Citrate, Sodium Lauryl Sulfate, Tartaric Acid

Principal Display Panel -Bottle Label

Target Up and Up

Earwax Removal Aid Drops

Carbamide Peroxide 6.5%

NET 0.5 FLOZ (15 ml)

Principal Display Panel - Carton -Drops

Target Up and Up NDC 11673-761-05

Earwax Removal Aid Drops

Carbamide Peroxide 6.5%

NET 0.5 FLOZ (15 ml)

Principal Display Panel -Carton -KIT

Target Up and Up NDC 11673-761-06

Earwax Removal KIT

Carbamide Peroxide 6.5%

NET 0.5 FLOZ (15 ml)